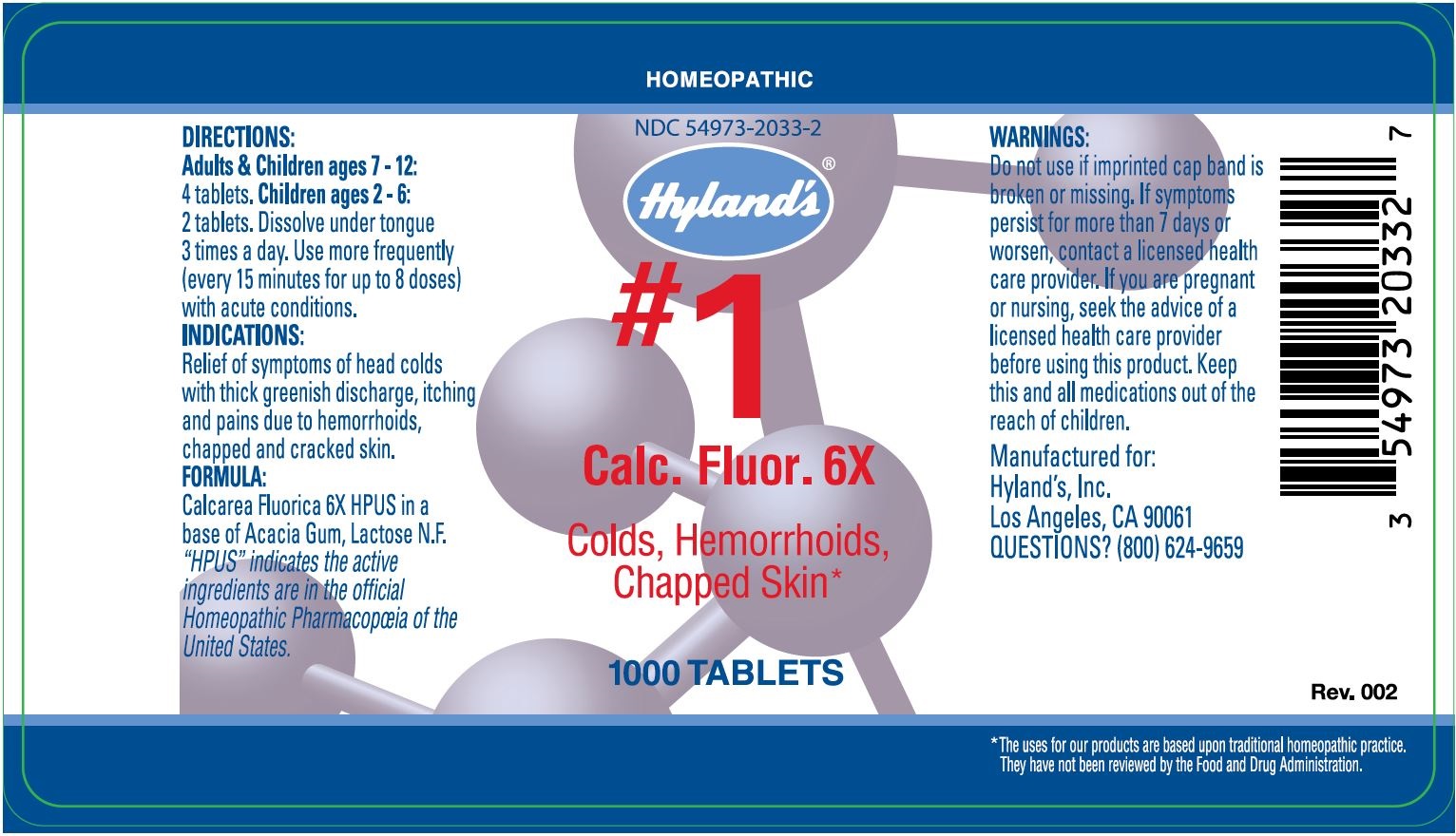 DRUG LABEL: CALC FLUOR
NDC: 54973-2033 | Form: TABLET
Manufacturer: Hyland's Inc.
Category: homeopathic | Type: HUMAN OTC DRUG LABEL
Date: 20221207

ACTIVE INGREDIENTS: CALCIUM FLUORIDE 6 [hp_X]/1 1
INACTIVE INGREDIENTS: LACTOSE; ACACIA

CALC FLUOR

DIRECTIONS

Adults & Children ages 6 - 12: 4 tablets. Children ages 2 - 6: 2 tablets. Dissolve under tongue 3 times a day. Use more frequently (every 15 minutes for up to 8 doses) with acute conditions.

PURPOSE

For Colds, Hemorrhoids, Chapped Skin

INDICATIONS

Relief of symptoms of headcolds with thick, greenish discharge. Relieves the symptoms of itching and burning pains due to hemorrhoids. Relieves the symptoms of chapped and cracked skin.

ACTIVE INGREDIENT

Calcarea Fluorica 6X HPUS

INACTIVE INGREDIENT

In a base of Acacia Gum, Lactose N.F.

“HPUS” indicates that the active ingredients are in the official Homeopathic Pharmacopœia of the United States.

Warnings

Do not use if imprinted cap band is broken or missing. If symptoms persist for more than 7 days or worsen, contact a licensed health care provider.

PREGNANCY OR BREAST FEEDING

If you are pregnant or nursing, seek the advice of a licensed health care provider before using this product.

KEEP OUT OF REACH OF CHILDREN

Keep all medications out of the reach of children.

QUESTIONS?

800.624.9659

PRINCIPAL DISPLAY PANEL - 1000 Tablet Bottle Label

HOMEOPATHIC

NDC 54973-2033-2

Hyland's®

#1

Calc. Fluor. 6X

Colds, Hemorrhoids,
Chapped Skin

1000 TABLETS